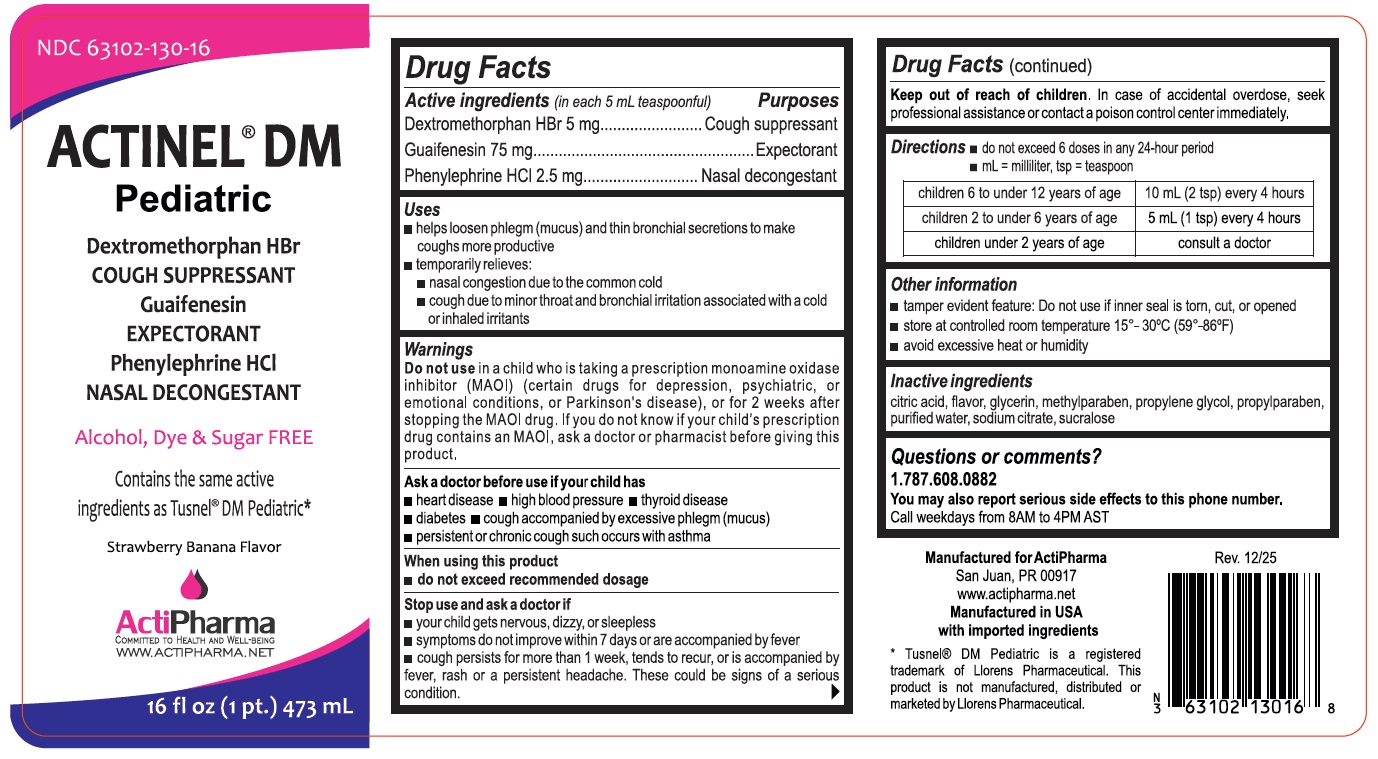 DRUG LABEL: ACTINEL DM Pediatric
NDC: 63102-130 | Form: LIQUID
Manufacturer: ACTIPHARMA, LLC
Category: otc | Type: HUMAN OTC DRUG LABEL
Date: 20260115

ACTIVE INGREDIENTS: DEXTROMETHORPHAN HYDROBROMIDE 5 mg/5 mL; GUAIFENESIN 75 mg/5 mL; PHENYLEPHRINE HYDROCHLORIDE 2.5 mg/5 mL
INACTIVE INGREDIENTS: CITRIC ACID MONOHYDRATE; GLYCERIN; METHYLPARABEN; PROPYLENE GLYCOL; PROPYLPARABEN; WATER; SODIUM CITRATE, UNSPECIFIED FORM; SUCRALOSE

ACTINEL® DM Pediatric

Active ingredients (in each 5 mL teaspoonful)

Dextromethorphan HBr 5 mg

Guaifenesin 75 mg

Phenylephrine HCl 2.5 mg

Purposes

Cough suppressant

Expectorant

Nasal decongestant

Uses

• helps loosen phlegm (mucus) and thin bronchial secretions to make coughs more productive

• temporarily relieves:
• nasal congestion due to the common cold
• cough due to minor throat and bronchial irritation associated with a cold or inhaled irritants

Warnings

Do not use in a child who is taking a prescription monoamine oxidase inhibitor (MAOI) (certain drugs for depression, psychiatric, or emotional conditions, or Parkinson’s disease), or for 2 weeks after stopping the MAOI drug. If you do not know if your child's prescription drug contains an MAOI, ask a doctor or pharmacist before giving this product.

Ask a doctor before use if your child has
• heart disease • high blood pressure • thyroid disease
• diabetes • cough accompanied by excessive phlegm (mucus)
• persistent or chronic cough such occurs with asthma

When using this product
• do not exceed recommended dosage

Stop use and ask a doctor if
• your child gets nervous, dizzy, or sleepless
• symptoms do not improve within 7 days or are accompanied by fever
• cough persists for more than 1 week, tends to recur, or is accompanied by fever, rash, or a persistent headache. These could be signs of a serious condition.

Keep out of reach of children. In case of accidental overdose, seek professional assistance or contact a poison control center immediately.

Directions

• do not exceed 6 doses in any 24-hour period

• mL = milliliter, tsp = teaspoon

children 6 to under 12 years of age | 10 mL (2 tsp) every 4 hours
children 2 to under 6 years of age | 5 mL (1 tsp) every 4 hours
children under 2 years of age | consult a doctor

Other information

• tamper evident feature: Do not use if inner seal is torn, cut, or opened

• store at controlled room temperature 15°- 30°C (59° - 86°F)

• avoid excessive heat or humidity.

Inactive ingredients

citric acid, flavor, glycerin, methylparaben, propylene glycol, propylparaben, purified water, sodium citrate, sucralose

Questions or comments?

1.787.608.0882

You may also report serious side effects to this phone number.

Call weekdays from 8AM to 4PM AST

Alcohol, Dye & Sugar FREE

Contains the same active ingredients as Tusnel® DM Pediatric*

ActiPharma
COMMITTED TO HEALTH AND WELL-BEING
WWW.ACTIPHARMA.NET

Manufactured for Actipharma
San Juan, PR 00917.

Manufactured in USA with imported ingredients

* Tusnel® DM Pediatric is a registered trademark of Llorens Pharmaceutical. This product is not manufactured, distributed or marketed by Llorens Pharmaceutical.